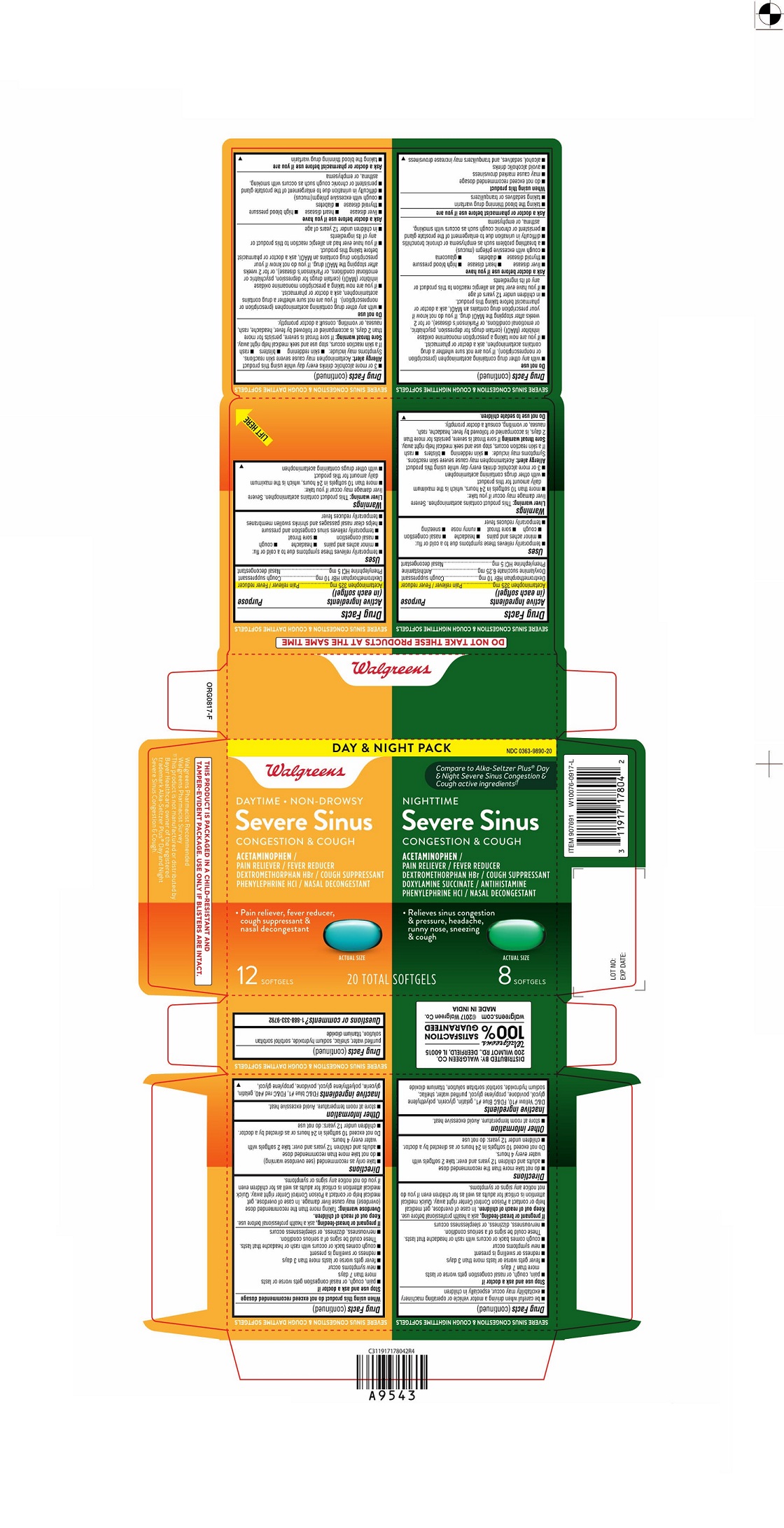 DRUG LABEL: SEVERE SINUS CONGESTION AND COUGH
NDC: 0363-9890 | Form: KIT | Route: ORAL
Manufacturer: Walgreens
Category: otc | Type: HUMAN OTC DRUG LABEL
Date: 20211130

ACTIVE INGREDIENTS: ACETAMINOPHEN 325 mg/1 1; DEXTROMETHORPHAN HYDROBROMIDE 10 mg/1 1; PHENYLEPHRINE HYDROCHLORIDE 5 mg/1 1; ACETAMINOPHEN 325 mg/1 1; DEXTROMETHORPHAN HYDROBROMIDE 10 mg/1 1; DOXYLAMINE SUCCINATE 6.25 mg/1 1; PHENYLEPHRINE HYDROCHLORIDE 5 mg/1 1
INACTIVE INGREDIENTS: FD&C BLUE NO. 1; FD&C RED NO. 40; GELATIN; GLYCERIN; POLYETHYLENE GLYCOL 400; POVIDONE K30; PROPYLENE GLYCOL; WATER; SHELLAC; SODIUM HYDROXIDE; TITANIUM DIOXIDE; POLYETHYLENE GLYCOL 400; POVIDONE K30; PROPYLENE GLYCOL; WATER; SHELLAC; SODIUM HYDROXIDE; TITANIUM DIOXIDE; D&C YELLOW NO. 10; FD&C BLUE NO. 1; GELATIN; GLYCERIN

SEVERE SINUS CONGESTION AND COUGH
DAYTIME NON-DROWSY / NIGHTIME

SEVERE SINUS CONGESTION & COUGH DAYTIME SOFTGELS

Drug Facts

ACTIVE INGREDIENT

Active Ingredients (in each softgel) | Purpose
Acetaminophen 325 mg | Pain reliever / Fever reducer
Dextromethorphan HBr 10 mg | Cough suppressant
Phenylephrine HCl 5 mg | Nasal decongestant

Uses

- temporarily relieves these symptoms due to a cold or flu:
  - minor aches and pains
  - headache
  - cough
  - nasal congestion
  - sore throat
  - temporarily relieves sinus congestion and pressure
- helps clear nasal passages and shrinks swollen membranes
- temporarily reduces fever

Warnings

Liver warning

This product contains acetaminophen. Severe liver damage may occur if you take:

- more than 10 softgels in 24 hours, which is the maximum daily amount for this product
- with other drugs containing acetaminophen
- 3 or more alcoholic drinks every day while using this product

Allergy Alert

Acetaminophen may cause severe skin reactions. Symptoms may include:

- skin reddening
- blisters
- rash

If a skin reaction occurs, stop use and seek medical help right away.

Sore throat warning

If sore throat is severe, persists for more than 2 days, is accompanied or followed by fever, headache, rash, nausea, or vomiting, consult a doctor promptly.

Do not use

- with any other drug containing acetaminophen (prescription or nonprescription). If you are not sure whether a drug contains acetaminophen, ask a doctor or pharmacist.
- if you are now taking a prescription monoamine oxidase inhibitor (MAOI) (certain drugs for depression, psychiatric or emotional conditions, or Parkinson's disease), or for 2 weeks after stopping the MAOI drug. If you do not know if your prescription drug contains an MAOI, ask a doctor or pharmacist before taking this product.
- If you have ever had an allergic reaction to this product or any of its ingredients
- In children under 12 years of age

Ask a doctor before use if you have

- liver disease
- heart disease
- high blood pressure
- thyroid disease
- diabetes
- cough with excessive phlegm(mucus)
- difficulty in urination due to enlargement of the prostate gland
- persistent or chronic cough such as occurs with smoking, asthma, or emphysema

Ask a doctor or pharmacist before use if you are

- taking the blood thinning drug warfarin

When using this product do not exceed recommended dosage

Stop use and ask a doctor if

- pain, cough or nasal congestion gets worse or lasts more than 7 days
- new symptoms occur
- fever gets worse or lasts more than 3 days
- redness or swelling is present
- cough comes back or occurs with rash or headache that lasts. These could be signs of a serious condition.
- nervousness, dizziness, or sleeplessness occurs.

PREGNANCY OR BREAST FEEDING

If pregnant or breast-feeding, ask a health professional before use.

Keep out of reach of children.

Overdose warning

Taking more than the recommended dose (overdose) may cause liver damage. In case of overdose, get medical help or contact a Poison Control Center right away. Quick medical attention is critical for adults as well as for children even if you do not notice any signs or symptoms.

Directions

- take only as recommended (see overdose warning)
- do not take more than recommended dose
- adults and children 12 years and over :take 2 softgels with water every 4 hours. Do not exceed 10 softgels in 24 hours or as directed by a doctor
- children under 12 years: do not use

Other Information

- store at room temperature. Avoid excessive heat.

Inactive ingredients

FD&C blue #1, FD&C red #40, gelatin, glycerin, polyethylene glycol, povidone, propylene glycol, purified water, shellac, sodium hydroxide, sorbitol sorbitan solution, titanium dioxide

Questions or comments?

1-888-333-9792

SEVERE SINUS CONGESTION & COUGH NIGHTTIME SOFTGELS

Drug Facts

ACTIVE INGREDIENT

Active Ingredients (in each softgel) | Purpose
Acetaminophen 325 mg | Pain reliever / Fever reducer
Dextromethorphan HBr 10 mg | Cough suppressant
Doxylamine succinate 6.25 mg | Antihistamine
Phenylephrine HCl 5 mg | Nasal decongestant

Uses

- temporarily relieves these symptoms due to a cold or flu:
  - minor aches and pains
  - headache
  - nasal congestion
  - cough
  - sore throat
  - runny nose
  - sneezing
- temporarily reduces fever

Warnings

Liver warning

This product contains acetaminophen. Severe liver damage may occur if you take:

- more than 10 softgels in 24 hours, which is the maximum daily amount for this product
- with other drugs containing acetaminophen
- 3 or more alcoholic drinks every day while using this product

Allergy Alert

Acetaminophen may cause severe skin reactions. Symptoms may include:

- skin reddening
- blisters
- rash

If a skin reaction occurs, stop use and seek medical help right away.

Sore throat warning

If sore throat is severe, persists for more than 2 days, is accompanied or followed by fever, headache, rash, nausea, or vomiting, consult a doctor promptly.

Do not use to sedate children.

Do not use

- with any other drug containing acetaminophen (prescription or nonprescription). If you are not sure whether a drug contains acetaminophen, ask a doctor or pharmacist.
- if you are now taking a prescription monoamine oxidase inhibitor (MAOI) (certain drugs for depression, psychiatric, or emotional conditions, or Parkinson's disease), or for 2 weeks after stopping the MAOI drug. If you do not know if your prescription drug contains an MAOI, ask a doctor or pharmacist before taking this product.
- in children under 12 years of age
- If you have ever had an allergic reaction to this product or any of its ingredients

Ask a doctor before use if you have

- liver disease
- heart disease
- high blood pressure
- thyroid disease
- diabetes
- glaucoma
- cough with excessive phlegm (mucus)
- a breathing problem such as emphysema or chronic bronchitis
- difficulty in urination due to enlargement of the prostate gland
- persistent or chronic cough such as occurs with smoking, asthma, or emphysema

Ask a doctor or pharmacist before use if you are

- taking the blood thinning drug warfarin
- taking sedatives or tranquilizers

When using this product

- do not exceed recommended dosage
- may cause marked drowsiness
- avoid alcoholic drinks
- alcohol, sedatives, and tranquilizers may increase drowsiness
- be careful when driving a motor vehicle or operating machinery
- excitability may occur, especially in children

Stop use and ask a doctor if

- pain, cough, or nasal congestion gets worse or lasts more than 7 days
- fever gets worse or lasts more than 3 days
- redness or swelling is present
- new symptoms occur
- cough comes back or occurs with rash or headache that lasts. These could be signs of a serious condition.
- nervousness, dizziness, or sleeplessness occurs

PREGNANCY OR BREAST FEEDING

If pregnant or breast-feeding, ask a health professional before use.

Keep out of reach of children. In case of overdose, get medical help or contact a Poison Control Center right away. Quick medical attention is critical for adults as well as for children even if you do not notice any signs or symptoms.

Directions

- do not take more than the recommended dose
- adults and children 12 years and over: take 2 softgels with water every 4 hours.

Do not exceed 10 softgels in 24 hours or as directed by a doctor.

- children under 12 years: do not use

Other information

- store at room temperature. Avoid excessive heat.

Inactive ingredients

D&C Yellow #10, FD&C Blue #1, gelatin, glycerin, polyethylene glycol, povidone, propylene glycol, purified water, shellac, sodium hydroxide, sorbitol sorbitan solution, titanium dioxide

PRINCIPAL DISPLAY PANEL - Kit Carton

DAY & NIGHT PACK

NDC 0363-9890-20

Walgreens

Compare to Alka-Seltzer PLUS® Day and Night Severe Sinus Congestion & Cough active ingredients‡‡

DAYTIMENON-DROWSY

Severe Sinus
Congestion & Cough

ACETAMINOPHEN/

PAIN RELIEVER/FEVER REDUCER

DEXTROMETHORPHAN HBr/COUGH SUPPRESSANT

PHENYLEPHRINE HCL/NASAL CONGESTANT

- Pain reliever, fever reducer,

cough suppressant &
nasal decongestant

Actual Size

12 SOFTGELS

NIGHTTIME

Severe Sinus
Congestion & Cough

ACETAMINOPHEN/

PAIN RELIEVER/FEVER REDUCER

DEXTROMETHORPHAN HBr/COUGH SUPPRESSANT

DOXYLAMINE SUCCINATE/ANTIHISTAMINE

PHENYLEPHRINE HCL/NASAL DECONGESTANT

- Relieves sinus congestion & pressure,
  headache, runny
  nose, sneezing &
  cough

Actual Size

8 SOFTGELS

20 TOTAL SOFTGELS